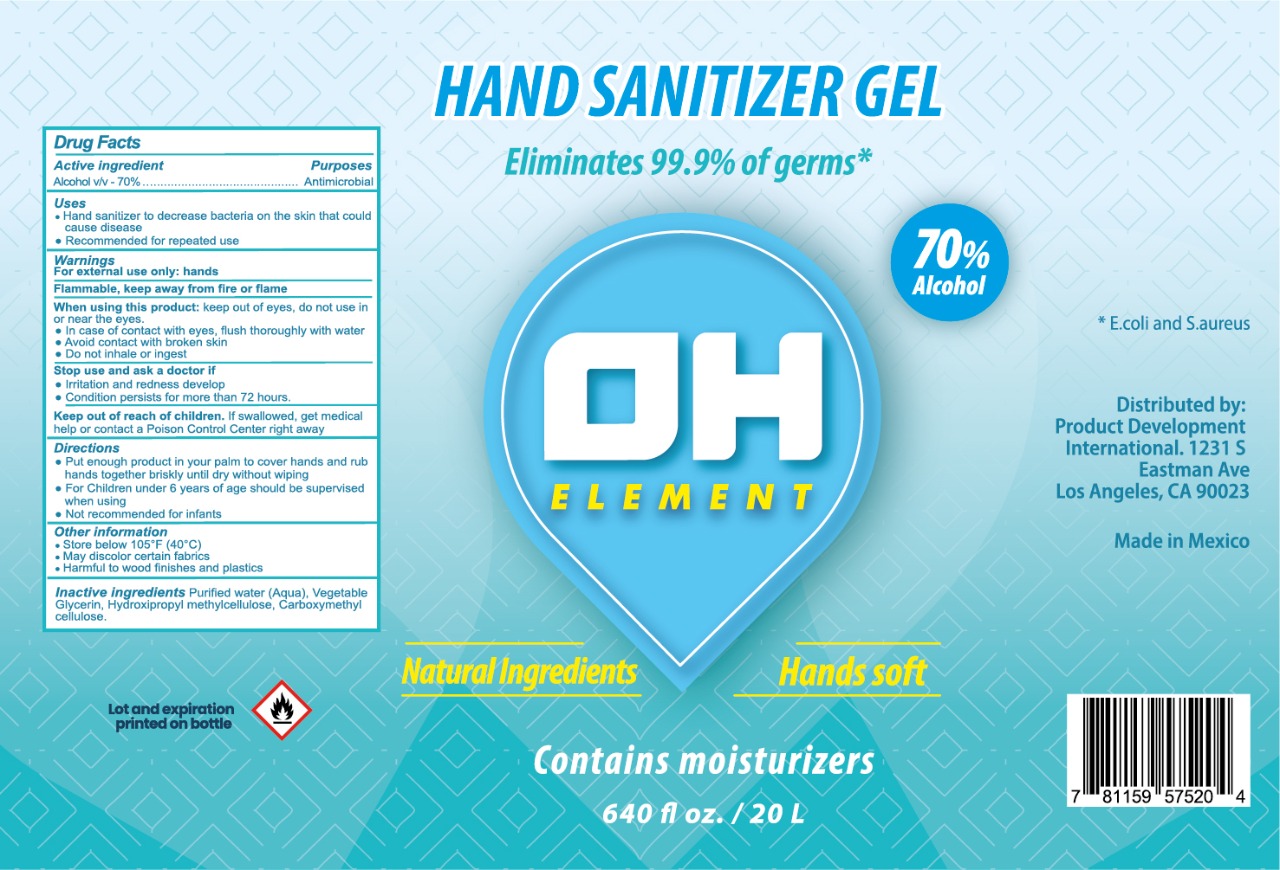 DRUG LABEL: HAND SANITIZER
NDC: 80535-0004 | Form: GEL
Manufacturer: FARMACIA SAN ARCANGEL, S.A DE C.V
Category: otc | Type: HUMAN OTC DRUG LABEL
Date: 20201029

ACTIVE INGREDIENTS: ALCOHOL 70 mL/100 mL
INACTIVE INGREDIENTS: WATER; CARBOXYMETHYLCELLULOSE; HYPROMELLOSE 2208 (60000 MPA.S); GLYCERIN

Active Ingredient

Alcohol v/v 70%

Purposes

Antimicrobial

Uses

Hand sanitizer to decrease bacteria on the skin that could cause disease

Recommended for repetead use

Warnings

for external use only: hands

flammable, keep away from fire and flame

When using this product

keep out of eyes, do not use in or near eyes.

-in case of contact with eyes flush thorougly with water

-avoid contact with broken skin

-do not inhale or ingest

when using this product

keep out of eyes, do not use in or near eyes.

-in case of contact with eyes flush thorougly with water

-avoid contact with broken skin

-do not inhale or ingest

Stop use and ask a doctor if

Irritation and redness develop

Condition persists for more than 72 hours

keep out of reach of children

if swallowed get medical help or contact a poison control center right away

Directions

put enough product in your palm to cover hands and rub hands together briskly until dry without wiping

for children uncer 6 years of age should be supervised when using

not recommended for infants

Other information

Store below 105 F (40 c)

may discolour certain fabrics

harmful to wood finishes and plastics

Inactive Ingredients

Purified water (aqua), Vegetable glycerin, Hydroxipropyl methylcellulose, carboxymethyl cellulose

Principal Display

Hand sanitizer gel

eliminates 99.9% of germs

70% alcohol

Natural ingredients hands soft

Contains moisturizers

640 fl oz/ 20 L